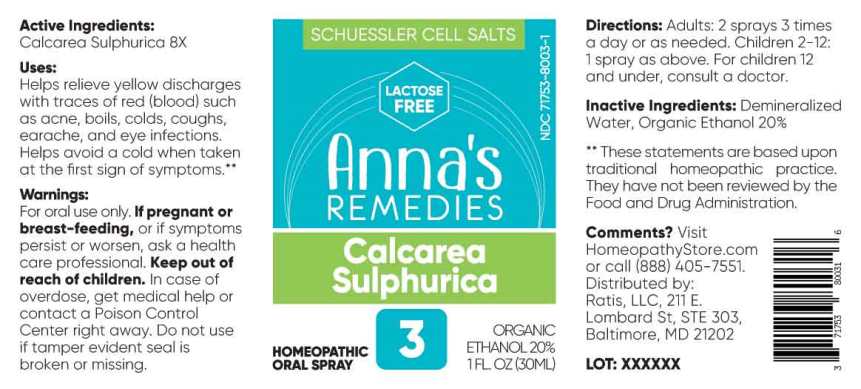 DRUG LABEL: Calcarea Sulphurica
NDC: 71753-8003 | Form: SPRAY
Manufacturer: Ratis, LLC
Category: homeopathic | Type: HUMAN OTC DRUG LABEL
Date: 20220120

ACTIVE INGREDIENTS: CALCIUM SULFATE ANHYDROUS 8 [hp_X]/1 mL
INACTIVE INGREDIENTS: WATER; ALCOHOL

Drug Facts:

ACTIVE INGREDIENT:

Calcarea Sulphurica 8X.

USES:

Helps relieve yellow discharges with traces of red (blood) such as acne, boils, colds, coughs, earache, and eye infections. Helps avoid a cold when taken at the first sign of symptoms.**

**These statements are based upon traditional homeopathic practice. They have not been reviewed by the Food and Drug Administration.

WARNINGS:

For oral use only.

If pregnant or breast-feeding, or if symptoms persist or worsen, ask a health care professional.

Keep out of reach of children. In case of overdose, get medical help or contact a Poison Control Center right away.

Do not use if tamper evident seal is broken or missing.

Keep out of reach of children. In case of overdose, get medical help or contact a Poison Control Center right away.

DIRECTIONS:

Adults: 2 sprays 3 times a day or as needed.

Children 2-12: 1 spray as above. For children 12 and under, consult a doctor.

INDICATIONS:

Helps relieve yellow discharges with traces of red (blood) such as acne, boils, colds, coughs, earache, and eye infections. Helps avoid a cold when taken at the first sign of symptoms.**

**These statements are based upon traditional homeopathic practice. They have not been reviewed by the Food and Drug Administration.

INACTIVE INGREDIENTS:

Demineralized Water, Organic Ethanol 20%

QUESTIONS:

Comments? Visit

HomeopathyStore.com

or call (888) 405-7551.

Distributed by:

Ratis, LLC,

211 E. Lombard St, STE 303,

Baltimore, MD 21202

PACKAGE LABEL DISPLAY:

NDC 71753-8003-1

LACTOSE FREE

Anna's

REMEDIES

Calcarea Sulphurica

HOMEOPATHIC ORAL SPRAY

1 FL. OZ (30ML)